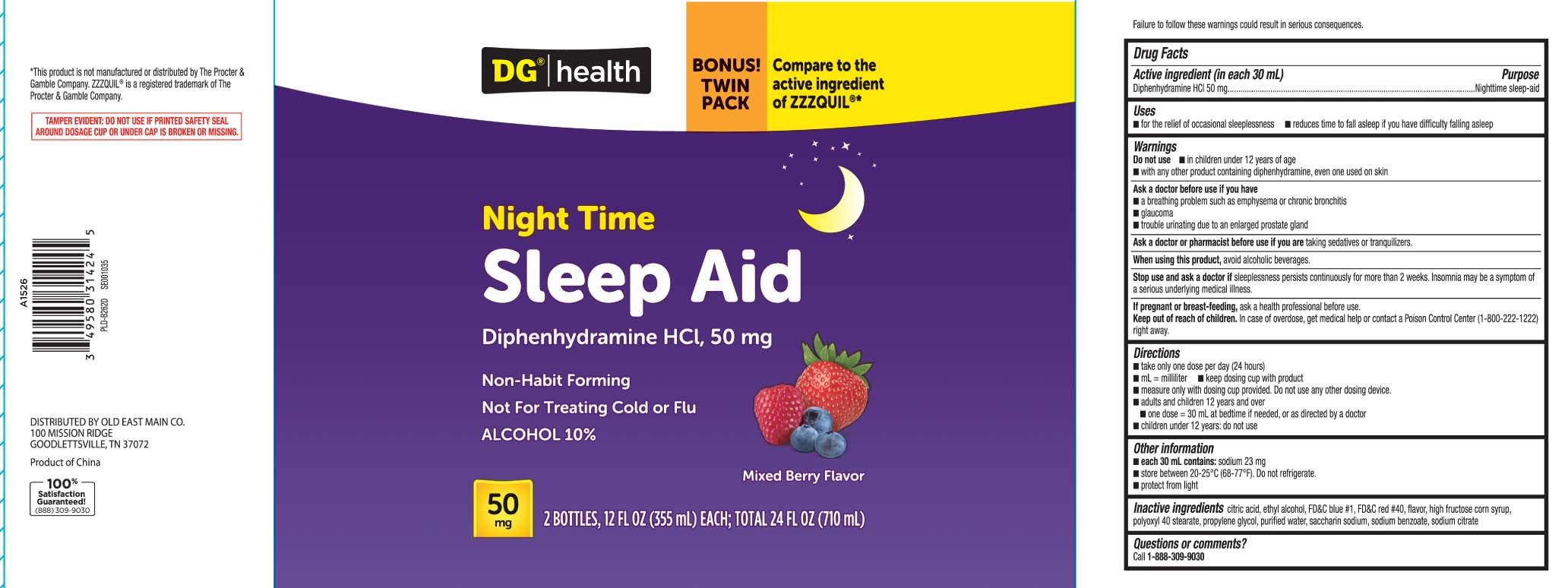 DRUG LABEL: Sleep Aid
NDC: 55910-981 | Form: LIQUID
Manufacturer: Dolgencorp, Inc.  (DOLLAR GENERAL & REXALL)
Category: otc | Type: HUMAN OTC DRUG LABEL
Date: 20260210

ACTIVE INGREDIENTS: DIPHENHYDRAMINE HYDROCHLORIDE 50 mg/30 mL
INACTIVE INGREDIENTS: ANHYDROUS CITRIC ACID; PROPYLENE GLYCOL; POLYOXYL STEARATE 40; WATER; SODIUM BENZOATE; SACCHARIN SODIUM ANHYDROUS; TRISODIUM CITRATE DIHYDRATE; HIGH FRUCTOSE CORN SYRUP; FD&C BLUE NO. 1; ALCOHOL; FD&C RED NO. 40

Drug Facts

Active ingredient (in each 30 mL)

Diphenhydramine HCl 50 mg

Purpose

Nighttime sleep-aid

Uses

- for the relief of occasional sleeplessness
- reduces time to fall asleep if you have difficulty falling asleep

Warnings

Do not use

- with any other product containing diphenhydramine, even one used on the skin
- in children under 12 years of age

Ask a doctor before use if you have

- a breathing problem such as asthma or emphysema or chronic bronchitis
- glaucoma
- trouble urinating due to an enlarged prostate gland

Ask a doctor or pharmacist before use if you are

taking sedatives or tranquilizers

When using this product

avoid alcoholic beverages

Stop use and ask a doctor if

sleeplessness persists continuously for more than 2 weeks. Insomnia may be a symptom of serious underlying medical illness.

If pregnant or breast-feeding,

ask a health professional before use.

Keep out of reach of children.

Overdose warning: In case of overdose, get medical help or contact a Poison Control Center (1-800-222-1222) right away.

Directions

- take only one dose per day (24 hours)
- mL=milliliter
- keep dosing cup with product
- measure only with dosing cup provided. Do not use any other dosing device.
- adults and children 12 years and over
  - one dose=30 mL at bedtime if needed, or as directed by a doctor
- children under 12 years do not use

Other information

- each 30 mL contains: sodium 23 mg
- store between 20-25ºC (68-77ºF). Do not refrigerate.
- protect from light

Inactive ingredients

citric acid, ethyl alcohol, FD&C blue #1, FD&C red #40, flavor, high fructose corn syrup, polyoxyl 40 stearate, propylene glycol, purified water, saccharin sodium , sodium benzoate, sodium citrate

Questions or comments?

Call 1-888-309-9030

Principal Display Panel

Compare to the active ingredient in ZzzQuil®*

Night Time

SLEEP-AID

Diphenhydramine HCl, 50 mg

Non-Habit Forming

Not For Treating Cold or Flu

ALCOHOL 10%

Berry Flavor

FL OZ (mL)

Failure to follow these warnings could result in serious consequences.

*This product is not manufactured or distributed by The Procter & Gamble Company. ZzzQuil® is a registered trademark of The Procter & Gamble Company.

TAMPER EVIDENT: DO NOT USE IF PRINTED SAFETY SEAL AROUND DOSAGE CUP OR UNDER CAP IS BROKEN OR MISSING.

DISTRIBUTED BY OLD EAST MAIN CO.

100 MISSION RIDGE,

GOODLETTSVILLE, TN 37072

Package Label

DOLLAR GENERAL HEALTH Nighttime Sleep Aid